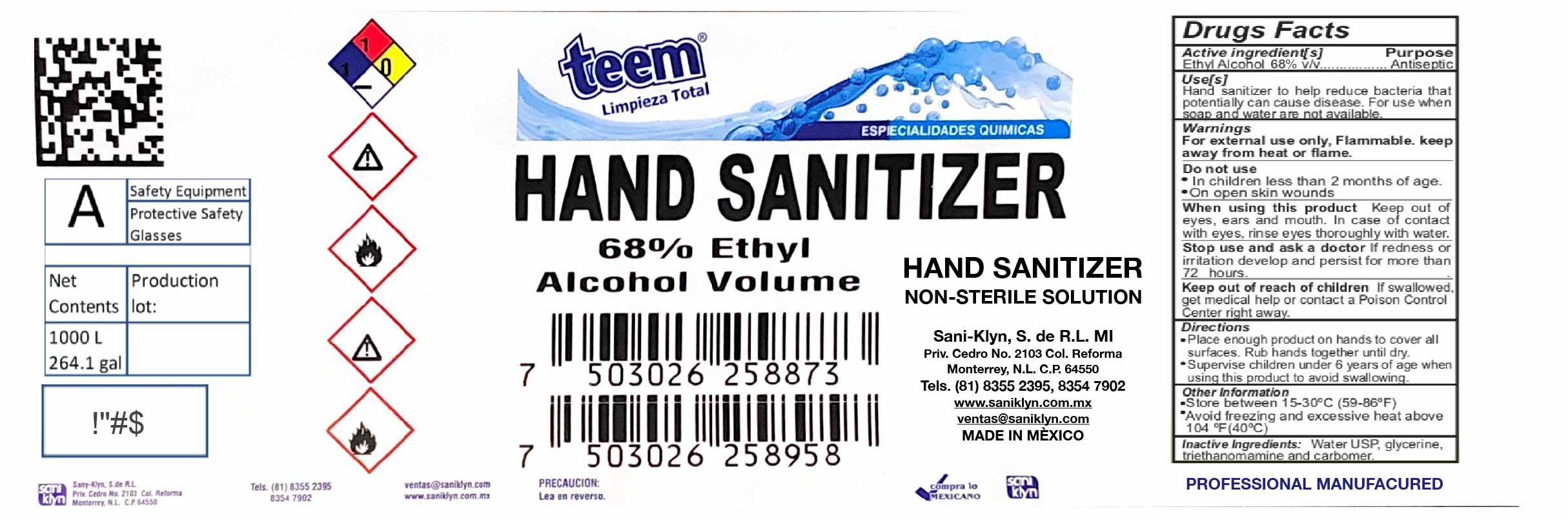 DRUG LABEL: Teem Hogar
NDC: 79004-005 | Form: GEL
Manufacturer: Saniklyn, S. de R.L. de M.I
Category: otc | Type: HUMAN OTC DRUG LABEL
Date: 20200813

ACTIVE INGREDIENTS: ALCOHOL 68 mL/100 mL
INACTIVE INGREDIENTS: WATER 30.45 mL/100 mL; CARBOMER 1342 0.4 mL/100 mL; TRIETHANOLAMINE HYDRIODIDE 0.4 mL/100 mL; GLYCERIN 0.75 mL/100 mL

ACTIVE INGREDIENT

Alcohol 68% v/v. Purpose: Antiseptic

PURPOSE

Antiseptic, Hand Sanitizer

USE IN SPECIFIC POPULATIONS

Hand Sanitizer to help reduce bacteria that potentially can use disease. For use when soap and water are not available.

WARNINGS

For external use only. Flammable. Keep away from heat or flame.

DO NOT USE

In children less than 2 months of age on open skin wounds.

When using this product keep out of eyes, ears, and mouth. In case of contact with eyes, rinse eyes thoroughly with water.

Stop use and ask a doctor if irritation or rash occurs. These may be signs of a serious condition.

Keep out of reach of children. If swallwed, get medical help or contact o Poison Control Center righ away.

Stop use and ask a doctor if irritation or rash occurs. These may be signs of a serious condition.

KEEP OUT OF REACH OF CHILDREN

Keep out reach of children. If sqallowed, get medical help or contact a Poison Control Center right away.

OTHER SAFETY INFORMATION

Store between 15-30C (59-86F)

Avoid freezing and excessive heat above 40C (104F)

INACTIVE INGREDIENT

Water USP, glycerin, triethalonamine and carbomer.

DOSAGE AND ADMINISTRATION

Place enough product on hands to cover all surfaces. Rub hands together until dry.

Supervise children under 6 years of age when using this product to avoid swallowing.

INDICATIONS AND USAGE

Place enough product on hands to cover all surfaces. Rub hands together until dry. Supervise children under 6 years of age when using this product to avoid swallowing.

PACKAGE LABEL

1000000 mL NDC: 79004-005-01